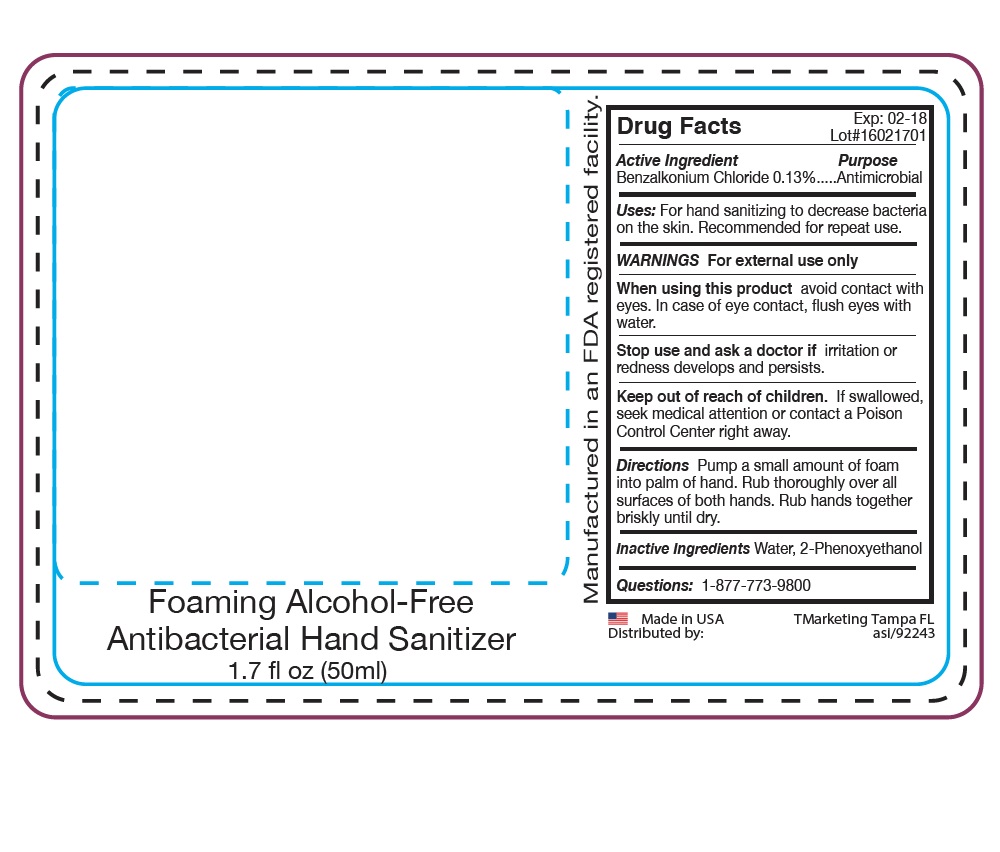 DRUG LABEL: Skin Crave non-alcohol Hand Sanitizer
NDC: 58418-786 | Form: SPRAY
Manufacturer: Tropical Enterprises International, Inc.
Category: otc | Type: HUMAN OTC DRUG LABEL
Date: 20170211

ACTIVE INGREDIENTS: BENZALKONIUM CHLORIDE 13 mg/1 mL
INACTIVE INGREDIENTS: 2-(2-(2-(2-PHENOXYETHOXY)ETHOXY)ETHOXY)ETHANOL

Antibacterial Non-Alcohol Hand Sanitizer Benzalkonium Spray

ACTIVE INGREDIENT

Benzalkonium Chloride 0.13%

DOSAGE AND ADMINISTRATION

Directions: Pump or spray a small amount of foam into palm of hand. Rub thoroughly over all surfaces of both hands. Rub hands together briskly until dry.

INACTIVE INGREDIENT

Water, 2-Phenoxyethanol

INDICATIONS AND USAGE

Uses: For hand sanitizing to decrease bacteria on the skin. Recommended for repeat use.

Keep out of reach of children. If swallowed, seek medical attention or contact a Poison Control Center right away.

OTC PURPOSE

Purpose... Antimicrobial

WARNINGS

WARNINGS For external use only